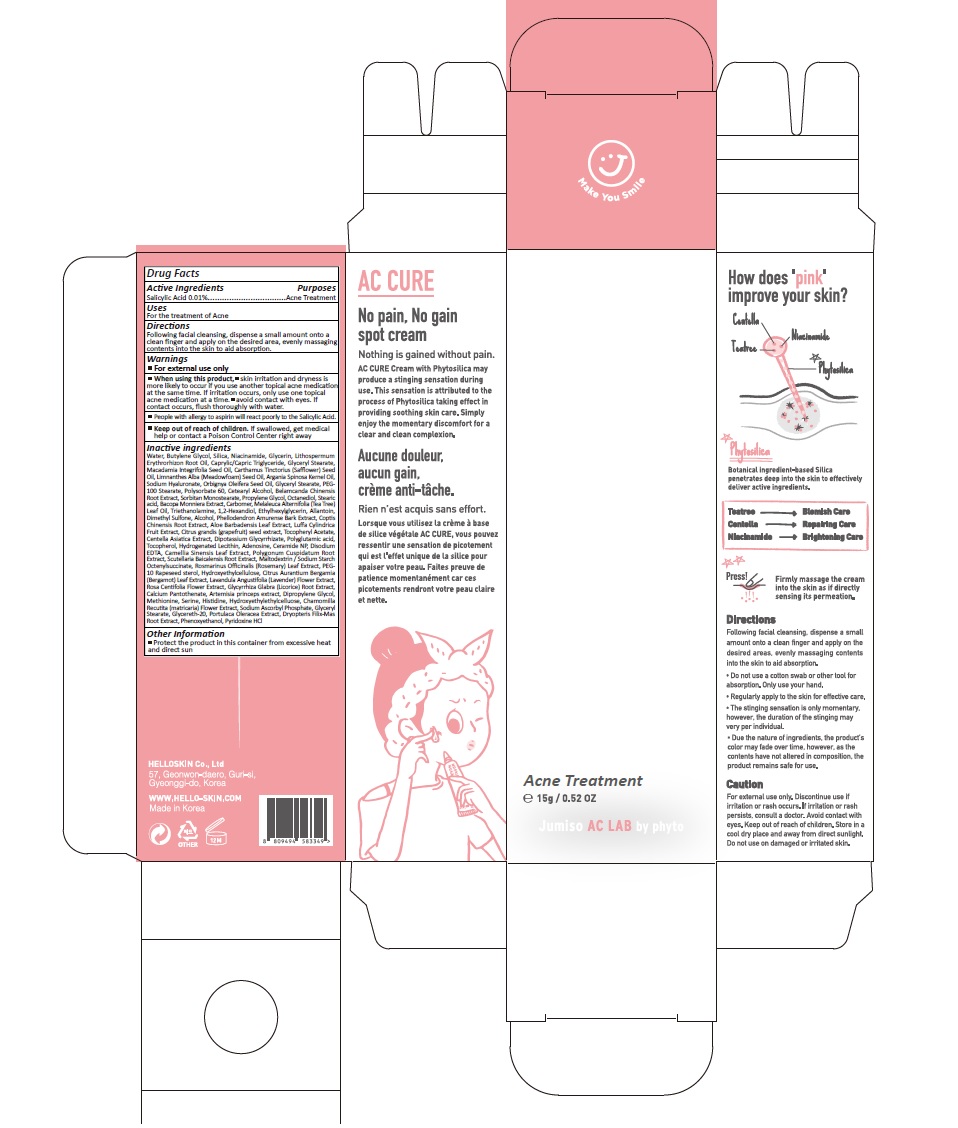 DRUG LABEL: JUMISO No pain No gain AC CURE spot
NDC: 73058-001 | Form: CREAM
Manufacturer: HELLO SKIN Co.,Ltd.
Category: otc | Type: HUMAN OTC DRUG LABEL
Date: 20190418

ACTIVE INGREDIENTS: SALICYLIC ACID 0.0015 g/15 g
INACTIVE INGREDIENTS: WATER; BUTYLENE GLYCOL; SILICON DIOXIDE; NIACINAMIDE; GLYCERIN; LITHOSPERMUM ERYTHRORHIZON ROOT; MEDIUM-CHAIN TRIGLYCERIDES; GLYCERYL MONOSTEARATE; MACADAMIA OIL; SAFFLOWER OIL; MEADOWFOAM SEED OIL; ARGAN OIL; HYALURONATE SODIUM; BABASSU OIL; PEG-100 STEARATE; POLYSORBATE 60; CETOSTEARYL ALCOHOL; IRIS DOMESTICA ROOT; SORBITAN MONOSTEARATE; PROPYLENE GLYCOL; OCTANEDIOL; STEARIC ACID; TEA TREE OIL; TROLAMINE; 1,2-HEXANEDIOL; ETHYLHEXYLGLYCERIN; ALLANTOIN; DIMETHYL SULFONE; ALCOHOL; PHELLODENDRON AMURENSE BARK; COPTIS CHINENSIS ROOT; ALOE VERA LEAF; LUFFA AEGYPTIACA FRUIT; CITRUS MAXIMA SEED; .ALPHA.-TOCOPHEROL ACETATE; CENTELLA ASIATICA; GLYCYRRHIZINATE DIPOTASSIUM; POLYGALIC ACID; TOCOPHEROL; HYDROGENATED SOYBEAN LECITHIN; ADENOSINE; CERAMIDE NP; EDETATE DISODIUM; GREEN TEA LEAF; REYNOUTRIA JAPONICA ROOT; SCUTELLARIA BAICALENSIS ROOT; ROSEMARY; PEG-10 RAPESEED STEROL; HYDROXYETHYL CELLULOSE (100 MPA.S AT 2%); CITRUS BERGAMIA LEAF; LAVANDULA ANGUSTIFOLIA SUBSP. ANGUSTIFOLIA FLOWER; ROSA CENTIFOLIA FLOWER; GLYCYRRHIZA GLABRA; CALCIUM PANTOTHENATE

73058-001

ACTIVE INGREDIENT

Salicylic Acid 0.01%

PURPOSE

Acne Treatment

INDICATIONS AND USAGE

For the treatment of Acne

DOSAGE AND ADMINISTRATION

Following facial cleansing, dispense a small amount onto a clean finger and apply on the desired area, evenly massaging contents into the skin to aid absorption.

WARNINGS

For external use only
When using this product, skin irritation and dryness is more likely to occur if you use another topical acne medication at the same time. If irritation occurs, only use one topical acne medication at a time. avoid contact with eyes. If contact occurs, flush thoroughly with water.

People with allergy to aspirin will react poorly to the Salicylic Acid.

KEEP OUT OF REACH OF CHILDREN

Keep out of reach of the children. If product is swallowed, get medical help or contact a poison control center right away.

INACTIVE INGREDIENT

Water, Butylene Glycol, Silica, Niacinamide, Glycerin, Lithospermum Erythrorhizon Root Oil, Caprylic/Capric Triglyceride, Glyceryl Stearate, Macadamia Integrifolia Seed Oil, Carthamus Tinctorius (Safflower) Seed Oil, Limnanthes Alba (Meadowfoam) Seed Oil, Argania Spinosa Kernel Oil, Sodium Hyaluronate, Orbignya Oleifera Seed Oil, Glyceryl Stearate, PEG-100 Stearate, Polysorbate 60, Cetearyl Alcohol, Belamcanda Chinensis Root Extract, Sorbitan Monostearate, Propylene Glycol, Octanediol, Stearic acid, Bacopa Monniera Extract, Carbomer, Melaleuca Alternifolia (Tea Tree) Leaf Oil, Triethanolamine, 1,2-Hexandiol, Ethylhexylglycerin, Allantoin, Dimethyl Sulfone, Alcohol, Phellodendron Amurense Bark Extract, Coptis Chinensis Root Extract, Aloe Barbadensis Leaf Extract, Luffa Cylindrica Fruit Extract, Citrus grandis (grapefruit) seed extract, Tocopheryl Acetate, Centella Asiatica Extract, Dipotassium Glycyrrhizate, Polyglutamic acid, Tocopherol, Hydrogenated Lecithin, Adenosine, Ceramide NP, Disodium EDTA, Camellia Sinensis Leaf Extract, Polygonum Cuspidatum Root Extract, Scutellaria Baicalensis Root Extract, Maltodextrin / Sodium Starch Octenylsuccinate, Rosmarinus Officinalis (Rosemary) Leaf Extract, PEG-10 Rapeseed sterol, Hydroxyethylcellulose, Citrus Aurantium Bergamia (Bergamot) Leaf Extract, Lavandula Angustifolia (Lavender) Flower Extract, Rosa Centifolia Flower Extract, Glycyrrhiza Glabra (Licorice) Root Extract, Calcium Pantothenate, Artemisia princeps extract, Dipropylene Glycol, Methionine, Serine, Histidine, Hydroxyethylethylcelluose, Chamomilla Recutita (matricaria) Flower Extract, Sodium Ascorbyl Phosphate, Glyceryl Stearate, Glycereth-20, Portulaca Oleracea Extract, Dryopteris Filix-Mas Root Extract, Phenoxyethanol, Pyridoxine HCl